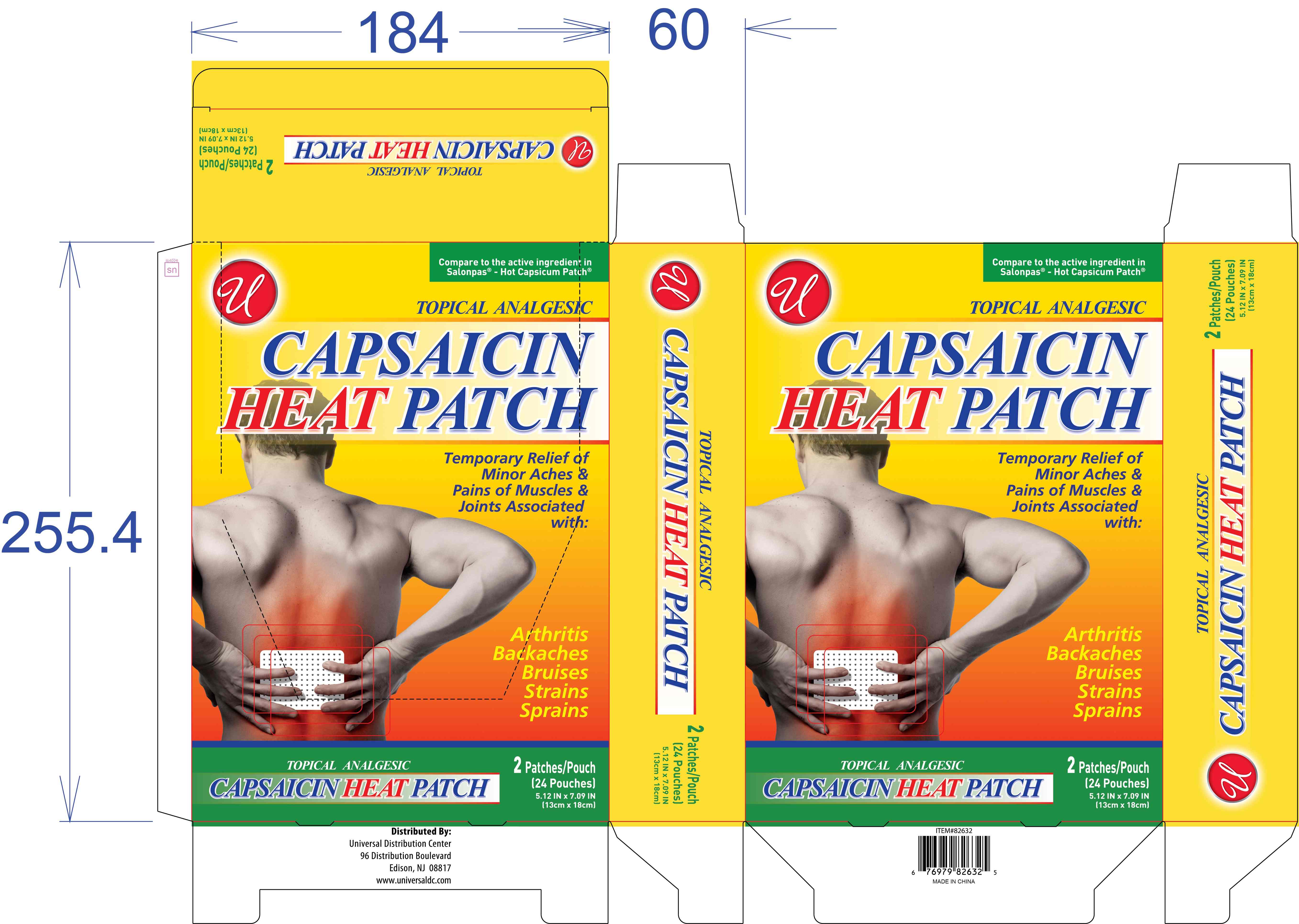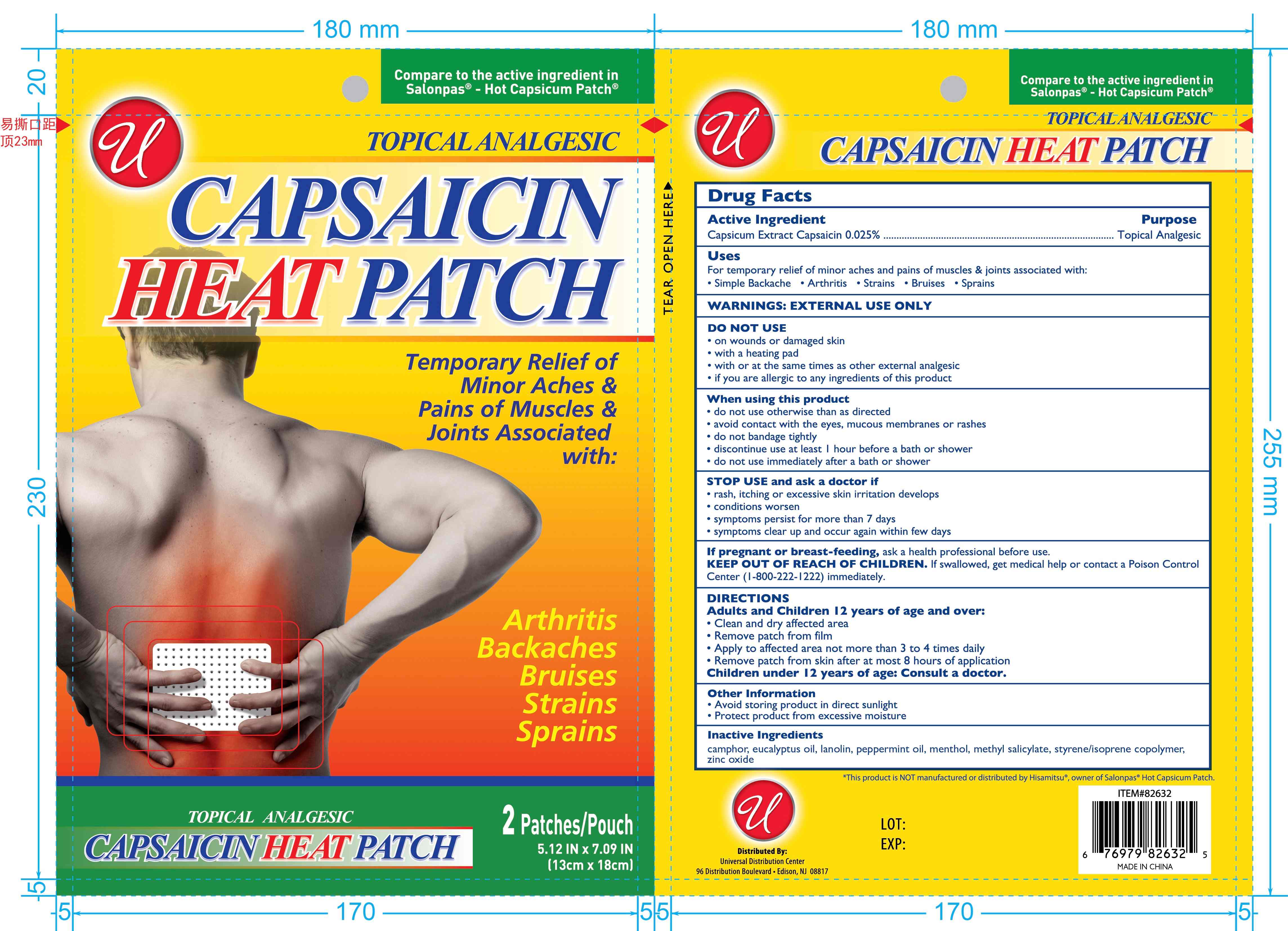 DRUG LABEL: CAPSAICIN HEAT Patch
NDC: 83559-013 | Form: PATCH
Manufacturer: Henan Enokon Medical Instrument Co., Ltd.
Category: otc | Type: HUMAN OTC DRUG LABEL
Date: 20260131

ACTIVE INGREDIENTS: CAPSAICIN 0.025 g/100 1
INACTIVE INGREDIENTS: CAMPHOR (SYNTHETIC); LANOLIN; STYRENE/ISOPRENE COPOLYMER (28:72; 210000 MW); MENTHOL, UNSPECIFIED FORM; EUCALYPTUS OIL; PEPPERMINT OIL; ZINC OXIDE; METHYL SALICYLATE

83559-013

Active Ingredient

Capsicum Extract Capsaicin 0.025%

Purpose

Topical Analgesic

Use

For temporary relief of minor aches and pains of muscles & joints associated with:
• Simple Backache • Arthritis • Strains • Bruises • Sprains

Warnings

EXTERNAL USE ONLY

Do not use

• on wounds or damaged skin
• with a heating pad
• with or at the same times as other external analgesic
• if you are allergic to any ingredients of this product

When Using

• do not use otherwise than as directed
• avoid contact with the eyes, mucous membranes or rashes
• do not bandage tightly
• discontinue use at least 1 hour before a bath or shower
• do not use immediately after a bath or shower

Stop Use

• rash, itching or excessive skin irritation develops
• conditions worsen
• symptoms persist for more than 7 days
• symptoms clear up and occur again within few days

Ask Doctor

If pregnant or breast-feeding, ask a health professional before use.
Children under 12 years of age: Consult a doctor.

Keep Out Of Reach Of Children

If swallowed, get medical help or contact a Poison Control Center (1-800-222-1222) immediately.

Directions

Adults and Children 12 years of age and over:
Clean and dry affected area
Remove patch from film
Apply to affected area not more than 3 to 4 times daily
Remove patch from skin after at most 8 hours of application

Other information

• Avoid storing product in direct sunlight
• Protect product from excessive moisture

Compare to the active ingredient in Salonpas® - Hot Capsicum Patch®

*This product is NOT manufactured or distributed by Hisamitsu®, owner of Salonpas® Hot Capsicum Patch.

Distributed By:

Universal Distribution Center

96 Distribution Boulevard • Edison, NJ 08817

MADE IN CHINA

www.universaldc.com

Inactive ingredients

camphor, eucalyptus oil, lanolin, peppermint oil, menthol, methyl salicylate, styrene/isoprene copolymer, zinc oxide

Questions

www.universaldc.com